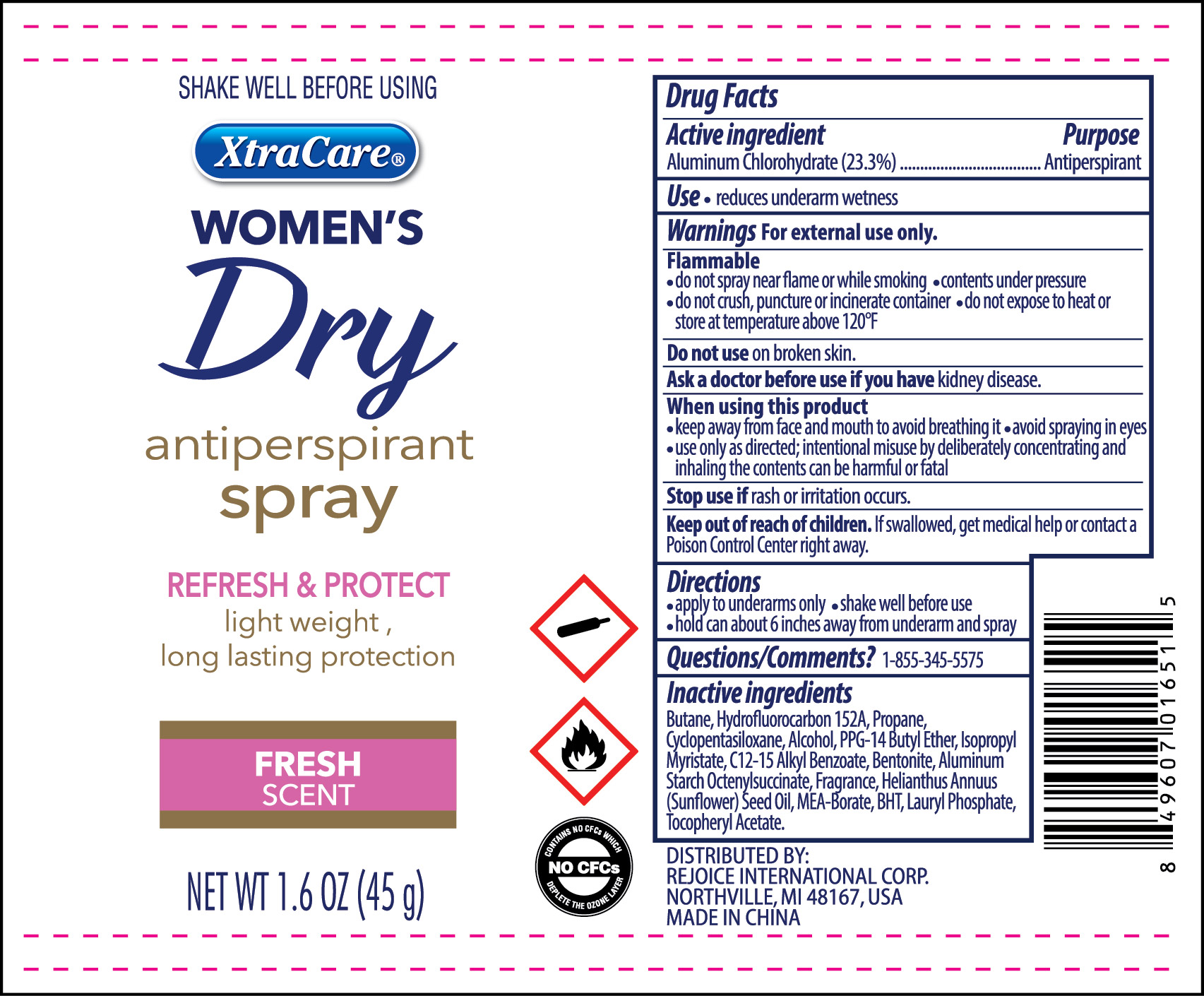 DRUG LABEL: Antiperspirant Dry 1.6 oz Lady
NDC: 57337-108 | Form: AEROSOL, SPRAY
Manufacturer: Rejoice International Inc.
Category: otc | Type: HUMAN OTC DRUG LABEL
Date: 20250213

ACTIVE INGREDIENTS: ALUMINUM CHLOROHYDRATE 23.3 g/100 g
INACTIVE INGREDIENTS: ALCOHOL; BUTYLATED HYDROXYTOLUENE; ISOBUTANE; 1,1-DIFLUOROETHANE; SUNFLOWER OIL; PROPANE; LAURYL PHOSPHATE; ISOPROPYL MYRISTATE; ALUMINUM STARCH OCTENYLSUCCINATE; DISTEARDIMONIUM HECTORITE; CYCLOMETHICONE 5; PPG-14 BUTYL ETHER; ALKYL (C12-15) BENZOATE

Antiperspirant Dry 1.6 oz Lady

Active Ingredient ........................................................................... Purpose

Aluminum Chlorohydrate 23.3% .................................................. Antiperspirant

PURPOSE

Antiperspirant

Keep out of reach of children. If swallowed, get medical help or contact a Poison Control Center right away.

INDICATIONS AND USAGE

Reduces underarm wetness

Warnings

For external use only.

Flammable.

Do not spray near flame or while smoking.
Contents under pressure
Do not crush, puncture or incinerate container.
Do not expose to heat or store at temperatures above 120oF
Do not use on broken skin.
Ask a doctor before using, if you have kidney disease.
When using this product
Keep away from face and mouth to avoid breathing it. Avoid spraying in eyes.
Use only directed. Intentional missuse by deliberately concentrating and inhaling the contents can be harmful or fatal
Stop use if rash or irritation develops.

Directions

- For underarm use only. Shake can well before each use. Hold can 6 inches away from skin. Spray underarm.

Inactive Ingredients

Isobutane, Butane, Hydrofluorocarbon 152a, Cyclopentasiloxane, Ethyl Alcohol, PPG-14 Butyl Ether, Helianthus Annuus Seed Oil, Isopropryl Myristate, C12-15 Alkyl Benzoate, Frangrance, Propane, Aluminum Starch Ocetenylsuccinate, Disteardimonium Hectorite, Dimethicone, Tocopheryl Acetate, BHT, Silica